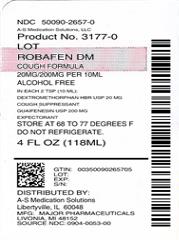 DRUG LABEL: Rabofen DM
NDC: 50090-2657 | Form: SOLUTION
Manufacturer: A-S Medication Solutions
Category: otc | Type: HUMAN OTC DRUG LABEL
Date: 20200118

ACTIVE INGREDIENTS: GUAIFENESIN 100 mg/5 mL; DEXTROMETHORPHAN HYDROBROMIDE 10 mg/5 mL
INACTIVE INGREDIENTS: SODIUM BENZOATE; SACCHARIN SODIUM; ANHYDROUS CITRIC ACID; GLYCERIN; MENTHOL, UNSPECIFIED FORM; WATER; CORN SYRUP; PRUNUS SEROTINA BARK; FD&C RED NO. 40

Rabofen™ DM

Drug Facts

ACTIVE INGREDIENT

PURPOSE

Active ingredients (in each 2 TSP (10 mL)) | Purposes
Dextromethorphan HBr, USP 20 mg | Cough suppressant
Guaifenesin, USP 200 mg | Expectorant

Uses

- temporarily relieves cough due to minor throat and bronchial irritation as may occur with a cold
- helps loosen phlegm (mucus) and thin bronchial secretions to drain bronchial tubes.

Warnings

Do not use if you are now taking a prescription monoamine oxidase inhibitor (MAOI) (certain drugs for depression, psychiatric or emotional conditions, or Parkinson's disease), or for 2 weeks after stopping the MAOI drug. If you do not know if your prescription drug contains an MAOI, ask a doctor or pharmacist before taking this product.

Ask a doctor before use if you have

- cough that lasts or is chronic such as occurs with smoking, asthma, chronic bronchitis or emphysema
- cough that occurs with too much phlegm (mucus).

Stop use and ask a doctor if cough lasts more than 7 days, comes back, or is accompanied by fever, rash, or persistent headache. These could be signs of a serious condition.

PREGNANCY OR BREAST FEEDING

If pregnant or breast-feeding, ask a health professional before use.

KEEP OUT OF REACH OF CHILDREN

Keep out of the reach of children. In case of overdose, get medical help or contact a Poison Control Center right away.

Directions

- do not take more than 6 doses in any 24-hour period
- use enclosed dosing cup only. Do not use any other device.
- this adult product is not intended for use in children under 12 years of age
- TSP=teaspoonful

adults and children 12 years and over | 2 TSP every 4 hours
children under 12 years | do not use

Other information

- each TSP (5 mL) contains: sodium 3 mg
- store at 20°-25°C (68°-77°F). Do not refrigerate

TAMPER-EVIDENT

Do not use this product if inner foil seal over the mouth of the bottle is cut, torn, broken or missing

Inactive ingredients

artificial cherry flavor, citric acid, corn syrup, FD&C Red #40, glycerin, menthol, purified water, saccharin sodium, sodium benzoate

Questions or comments?

(800)-616-2471

Distributed by:
MAJOR® PHARMACEUTICALS
17177 N Laurel Park Drive,
Suite 233, Livonia, MI 48152

HOW SUPPLIED

Product: 50090-2657

NDC: 50090-2657-0 118 mL in a BOTTLE